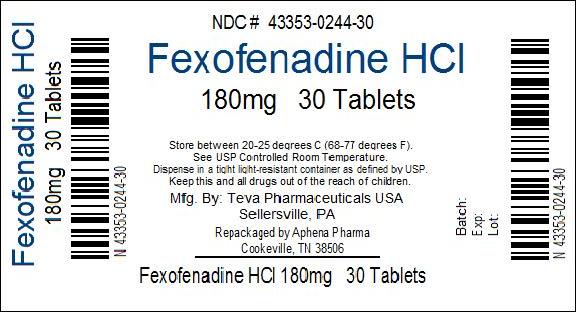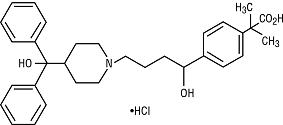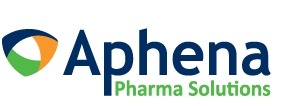 DRUG LABEL: Fexofenadine Hydrochloride
NDC: 43353-244 | Form: TABLET, FILM COATED
Manufacturer: Aphena Pharma Solutions - Tennessee, Inc.
Category: prescription | Type: HUMAN PRESCRIPTION DRUG LABEL
Date: 20120716

ACTIVE INGREDIENTS: FEXOFENADINE HYDROCHLORIDE 180 mg/1 1
INACTIVE INGREDIENTS: COLLOIDAL SILICON DIOXIDE; CROSCARMELLOSE SODIUM; HYPROMELLOSES; FERROSOFERRIC OXIDE; FERRIC OXIDE RED; FERRIC OXIDE YELLOW; LACTOSE MONOHYDRATE; MAGNESIUM STEARATE; CELLULOSE, MICROCRYSTALLINE; POLYETHYLENE GLYCOLS; POVIDONE; TITANIUM DIOXIDE

HIGHLIGHTS OF PRESCRIBING INFORMATION

These highlights do not include all the information needed to use fexofenadine hydrochloride tablets USP safely and effectively. See full prescribing information for fexofenadine hydrochloride tablets USP.
Fexofenadine hydrochloride tablets USP for oral use.
Initial U.S. Approval: 1996

1 INDICATIONS AND USAGE

Fexofenadine hydrochloride is an H1-receptor antagonist indicated for:

- Relief of symptoms associated with seasonal allergic rhinitis in patients ≥ 2 years of age (1.1)
- Treatment of uncomplicated skin manifestations of chronic idiopathic urticaria in patients ≥ 6 months of age (1.2)

2 DOSAGE AND ADMINISTRATION

Patient Population | Fexofenadine Hydrochloride Tablets USP (2.1)
Adults and children ≥ 12 years | 60 mg twice daily [starting dose in patients with decreased renal function should be the recommended dose indicated above but administered once daily] or 180 mg once daily [dose not for use in patients with decreased renal function]
Children 6 to 11 years | 30 mg twice daily
Children 2 to 5 years | N/A
Children 6 months to less than 2 years | N/A

- Fexofenadine hydrochloride tablets USP: take with water (2.1)

3 DOSAGE FORMS AND STRENGTHS

- Fexofenadine hydrochloride tablets USP: 30 mg, 60 mg, and 180 mg (3)

4 CONTRAINDICATIONS

Patients with known hypersensitivity to fexofenadine and any of the ingredients of fexofenadine hydrochloride tablets. (4)

6 ADVERSE REACTIONS

The most common adverse reactions (≥ 2%) in subjects age 12 years and older were headache, back pain, dizziness, stomach discomfort, and pain in extremity. In subjects aged 6 to 11 years, cough, upper respiratory tract infection, pyrexia and otitis media were more frequently reported. In subjects aged 6 months to 5 years, vomiting, diarrhea, somnolence/fatigue and rhinorrhea were more frequently reported. (6.1) Other adverse reactions have been reported. (6)

To report SUSPECTED ADVERSE REACTIONS, contact TEVA USA, PHARMACOVIGILANCE at tel: 1-888-838-2872, X6351 and drug.safety@tevausa.com or FDA at 1-800-FDA-1088 or www.fda.gov/medwatch

7 DRUG INTERACTIONS

- Antacids: Do not take at the same time as aluminum and magnesium containing antacids (7.1)
- Fruit juice: Take with water; not fruit juice

8 USE IN SPECIFIC POPULATIONS

- Pregnancy: Use only if benefit justifies risk to fetus (8.1)
- Nursing Mothers: Use with caution (8.3)

FULL PRESCRIBING INFORMATION

1 INDICATIONS AND USAGE

1.1 Seasonal Allergic Rhinitis

Fexofenadine hydrochloride tablets are indicated for the relief of symptoms associated with seasonal allergic rhinitis in adults and children 2 years of age and older.

1.2 Chronic Idiopathic Urticaria

Fexofenadine hydrochloride tablets are indicated for treatment of uncomplicated skin manifestations of chronic idiopathic urticaria in adults and children 6 months of age and older.

2 DOSAGE AND ADMINISTRATION

2.1 Fexofenadine Hydrochloride Tablets USP

Seasonal Allergic Rhinitis and Chronic Idiopathic Urticaria

Adults and Children 12 Years and Older: The recommended dose of fexofenadine hydrochloride tablets USP are 60 mg twice daily or 180 mg once daily with water. A dose of 60 mg once daily is recommended as the starting dose in patients with decreased renal function [see Clinical Pharmacology (12.3)].

Children 6 to 11 Years: The recommended dose of fexofenadine hydrochloride tablets USP are 30 mg twice daily with water. A dose of 30 mg once daily is recommended as the starting dose in pediatric patients with decreased renal function [see Clinical Pharmacology (12.3)].

3 DOSAGE FORMS AND STRENGTHS

Fexofenadine hydrochloride tablets USP are available in 30 mg, 60 mg, and 180 mg strengths. Fexofenadine hydrochloride tablets USP are coated with a peach colored film coating. Tablets have the following unique shape and identifiers: 30 mg tablets are capsule-shaped and have “93” on one side and “7251” on the other; 60 mg tablets are round and have “93” on one side and “7252” on the other; and 180 mg tablets are round and have “93” on one side and “7253” on the other.

4 CONTRAINDICATIONS

Fexofenadine hydrochloride tablets are contraindicated in patients with known hypersensitivity to fexofenadine and any of the ingredients of fexofenadine hydrochloride tablets. Rare cases of hypersensitivity reactions with manifestations such as angioedema, chest tightness, dyspnea, flushing and systemic anaphylaxis have been reported.

6 ADVERSE REACTIONS

6.1 Clinical Studies Experience

Because clinical trials are conducted under widely varying conditions, adverse reaction rates observed in the clinical trials of a drug cannot be directly compared to rates in the clinical trials of another drug and may not reflect the rates observed in practice.

The safety data described below reflect exposure to fexofenadine hydrochloride in 5083 patients in trials for allergic rhinitis and chronic idiopathic urticaria. In these trials, 3010 patients 12 years of age and older with seasonal allergic rhinitis were exposed to fexofenadine hydrochloride at doses of 20 to 240 mg twice daily or 120 to 180 mg once daily. A total of 646 patients 6 to 11 years of age with seasonal allergic rhinitis were exposed to fexofenadine hydrochloride at doses of 15 to 60 mg twice daily. The duration of treatment in these trials was 2 weeks. A total of 534 patients 6 months to 5 years of age with allergic rhinitis were exposed to fexofenadine hydrochloride at doses of 15 to 30 mg twice daily. The duration of treatment in these trials ranged from 1 day to 2 weeks. There were 893 patients 12 years of age and older with chronic idiopathic urticaria exposed to fexofenadine hydrochloride at doses of 20 to 240 mg twice daily or 180 mg once daily. The duration of treatment in these trials was 4 weeks.

Seasonal Allergic Rhinitis

Adults and Adolescents: In placebo-controlled seasonal allergic rhinitis clinical trials in subjects 12 years of age and older, 2439 subjects received fexofenadine hydrochloride capsules at doses of 20 mg to 240 mg twice daily. All adverse reactions that were reported by greater than 1% of subjects who received the recommended daily dose of fexofenadine hydrochloride (60 mg capsules twice daily) are listed in Table 1.

In another placebo-controlled clinical study in the United States, 571 subjects aged 12 years and older received fexofenadine hydrochloride tablets at doses of 120 or 180 mg once daily. Table 1 also lists adverse reactions that were reported by greater than 2% of subjects treated with fexofenadine hydrochloride tablets at doses of 180 mg once daily.

The incidence of adverse reactions, including somnolence/fatigue, was not dose-related and was similar across subgroups defined by age, gender, and race.

Table 1: Adverse Reactions in Subjects Aged 12 Years and Older Reported in Placebo-Controlled Seasonal Allergic Rhinitis Clinical Trials in the United States
Twice-daily dosing with fexofenadine capsules at rates of greater than 1%
Adverse reaction | Fexofenadine 60 mg Twice Daily (n = 680) Frequency | Placebo Twice Daily (n = 674) Frequency
Dysmenorrhea | 1.5% | 0.3%
Once-daily dosing with fexofenadine hydrochloride tablets at rates of greater than 2%
Adverse reaction | Fexofenadine 180 mg Once Daily (n = 283) Frequency | Placebo (n = 293) Frequency
Headache | 10.3% | 7.2%
Back Pain | 2.5% | 1.4%

The frequency and magnitude of laboratory abnormalities were similar in fexofenadine hydrochloride- and placebo-treated subjects.

Pediatrics: Table 2 lists adverse reactions in subjects aged 6 years to 11 years of age which were reported by greater than 2% of subjects treated with fexofenadine hydrochloride tablets at a dose of 30 mg twice daily in placebo-controlled seasonal allergic rhinitis studies in the United States and Canada.

Table 2: Adverse Reactions Reported in Placebo-Controlled Seasonal Allergic Rhinitis Studies in Pediatric Subjects Aged 6 Years to 11 Years in the United States and Canada at Rates of Greater Than 2%
Adverse reaction | Fexofenadine 30 mg Twice Daily (n = 209) Frequency | Placebo (n = 229) Frequency
Cough | 3.8% | 1.3%
Upper Respiratory Tract Infection | 2.9% | 0.9%
Pyrexia | 2.4% | 0.9%
Otitis Media | 2.4% | 0.0%

Table 3 lists adverse reactions in subjects 6 months to 5 years of age which were reported by greater than 2% of subjects treated with fexofenadine hydrochloride in 3 open single- and multiple-dose pharmacokinetic studies and 3 placebo-controlled safety studies with fexofenadine hydrochloride capsule content (484 subjects) and suspension (50 subjects) at doses of 15 mg (108 subjects) and 30 mg (426 subjects) given twice a day.

Table 3: Adverse Reactions Reported in Placebo-Controlled Studies in Pediatric Subjects With Allergic Rhinitis Aged 6 Months to 5 Years of Age at Rates Greater Than 2%
Adverse reaction | Fexofenadine 15 mg Twice Daily (n = 108) Frequency | Fexofenadine 30 mg Twice Daily (n = 426) Frequency | Fexofenadine Total Twice Daily (n = 534) Frequency | Placebo (n = 430) Frequency
Vomiting | 12.0% | 4.2% | 5.8% | 8.6%
Diarrhea | 3.7% | 2.8% | 3.0% | 2.6%
Somnolence/Fatigue | 2.8% | 0.9% | 1.3% | 0.2%
Rhinorrhea | 0.9% | 2.1% | 1.9% | 0.9%

Chronic Idiopathic Urticaria

Adverse reactions reported by subjects 12 years of age and older in placebo-controlled chronic idiopathic urticaria studies were similar to those reported in placebo-controlled seasonal allergic rhinitis studies.

In placebo-controlled chronic idiopathic urticaria clinical trials, 726 subjects 12 years of age and older received fexofenadine hydrochloride tablets at doses of 20 to 240 mg twice daily. Table 4 lists adverse reactions in subjects aged 12 years and older which were reported by greater than 2% of subjects treated with fexofenadine hydrochloride 60 mg tablets twice daily in controlled clinical studies in the United States and Canada.

In a placebo-controlled clinical study in the United States, 167 subjects aged 12 years and older received fexofenadine hydrochloride 180 mg tablets. Table 4 also lists adverse reactions that were reported by greater than 2% of subjects treated with fexofenadine hydrochloride tablets at doses of 180 mg once daily.

Table 4: Adverse Reactions Reported in Subjects 12 Years of Age and Older in Placebo-Controlled Chronic Idiopathic Urticaria Studies
Twice-daily dosing with fexofenadine hydrochloride in studies in the United States and Canada at rates of greater than 2%
Adverse reaction | Fexofenadine 60 mg Twice Daily (n = 191) Frequency | Placebo (n = 183) Frequency
Dizziness | 2.1% | 1.1%
Back Pain | 2.1% | 1.1%
Stomach discomfort | 2.1% | 0.6%
Pain in extremity | 2.1% | 0.0%
Once-daily dosing with fexofenadine hydrochloride in a study in the United States at rates of greater than 2%
Adverse reaction | Fexofenadine 180 mg Once Daily (n = 167) Frequency | Placebo (n = 92) Frequency
Headache | 4.8% | 3.3%

The safety of fexofenadine hydrochloride in the treatment of chronic idiopathic urticaria in pediatric patients 6 months to 11 years of age is based on the safety profile of fexofenadine hydrochloride in adults and pediatric patients at doses equal to or higher than the recommended dose [see Use in Specific Populations (8.4)].

6.2 Postmarketing Experience

In addition to the adverse reactions reported during clinical studies and listed above, the following adverse events have been identified during post-approval use of fexofenadine hydrochloride. Because these events are reported voluntarily from a population of uncertain size, it is not always possible to reliably estimate their frequency or establish a causal relationship to drug exposure. Events that have been reported rarely during postmarketing experience include: insomnia, nervousness, sleep disorders or paroniria, and hypersensitivity reactions (including anaphylaxis, urticaria, angioedema, chest tightness, dyspnea, flushing, pruritus, and rash).

7 DRUG INTERACTIONS

7.1 Antacids

Fexofenadine hydrochloride should not be taken closely in time with aluminum and magnesium containing antacids. In healthy adult subjects, administration of 120 mg of fexofenadine hydrochloride (2 x 60 mg capsule) within 15 minutes of an aluminum and magnesium containing antacid (Maalox®) decreased fexofenadine AUC by 41% and Cmax by 43%.

7.2 Erythromycin and Ketoconazole

Fexofenadine has been shown to exhibit minimal (ca. 5%) metabolism. However, coadministration of fexofenadine hydrochloride with either ketoconazole or erythromycin led to increased plasma concentrations of fexofenadine in healthy adult subjects. Fexofenadine had no effect on the pharmacokinetics of either erythromycin or ketoconazole. In 2 separate studies in healthy adult subjects, fexofenadine hydrochloride 120 mg twice daily (240 mg total daily dose) was coadministered with either erythromycin 500 mg every 8 hours or ketoconazole 400 mg once daily under steady-state conditions to healthy adult subjects (n = 24, each study). No differences in adverse events or QTc interval were observed when subjects were administered fexofenadine hydrochloride alone or in combination with either erythromycin or ketoconazole. The findings of these studies are summarized in the following table:

Table 5: Effects on Steady-State Fexofenadine Pharmacokinetics After 7 Days of Coadministration With Fexofenadine Hydrochloride 120 mg Every 12 Hours in Healthy Adult Subjects (n = 24)
Concomitant Drug | CmaxSS (Peak plasma concentration) | AUCss(0-12h) (Extent of systemic exposure)
Erythromycin (500 mg every 8 hrs) | +82% | +109%
Ketoconazole (400 mg once daily) | +135% | +164%

The changes in plasma levels were within the range of plasma levels achieved in adequate and well-controlled clinical trials.

The mechanism of these interactions has been evaluated in in vitro, in situ, and in vivo animal models. These studies indicate that ketoconazole or erythromycin coadministration enhances fexofenadine gastrointestinal absorption. This observed increase in the bioavailability of fexofenadine may be due to transport-related effects, such as p-glycoprotein. In vivo animal studies also suggest that in addition to enhancing absorption, ketoconazole decreases fexofenadine gastrointestinal secretion, while erythromycin may also decrease biliary excretion.

7.3 Fruit Juices

Fruit juices such as grapefruit, orange and apple may reduce the bioavailability and exposure of fexofenadine. This is based on the results from 3 clinical studies using histamine induced skin wheals and flares coupled with population pharmacokinetic analysis. The size of wheal and flare were significantly larger when fexofenadine hydrochloride was administered with either grapefruit or orange juices compared to water. Based on the literature reports, the same effects may be extrapolated to other fruit juices such as apple juice. The clinical significance of these observations is unknown. In addition, based on the population pharmacokinetics analysis of the combined data from grapefruit and orange juices studies with the data from a bioequivalence study, the bioavailability of fexofenadine was reduced by 36%. Therefore, to maximize the effects of fexofenadine, it is recommended that fexofenadine hydrochloride tablets should be taken with water [see Clinical Pharmacology (12.3) and Dosage and Administration (2.1)].

8 USE IN SPECIFIC POPULATIONS

8.1 Pregnancy

Teratogenic Effects

Pregnancy Category C. There was no evidence of teratogenicity in rats or rabbits at oral doses of terfenadine up to 300 mg/kg (which led to fexofenadine exposures that were approximately 4 and 30 times, respectively, the exposure at the maximum recommended human daily oral dose of 180 mg of fexofenadine hydrochloride based on comparison of AUCs).

In mice, no adverse effects and no teratogenic effects during gestation were observed with fexofenadine hydrochloride at oral doses up to 3730 mg/kg (which led to fexofenadine exposures that were approximately 15 times the exposure at the maximum recommended human daily oral dose of 180 mg of fexofenadine hydrochloride based on comparison of AUCs).

There are no adequate and well controlled studies in pregnant women. Fexofenadine hydrochloride should be used during pregnancy only if the potential benefit justifies the potential risk to the fetus.

Nonteratogenic Effects

Dose-related decreases in pup weight gain and survival were observed in rats exposed to an oral dose of 150 mg/kg of terfenadine (which led to fexofenadine exposures that were approximately 3 times the exposure at the maximum recommended human daily oral dose of 180 mg of fexofenadine hydrochloride based on comparison of AUCs).

8.3 Nursing Mothers

It is not known if fexofenadine is excreted in human milk. There are no adequate and well-controlled studies in women during lactation. Because many drugs are excreted in human milk, caution should be exercised when fexofenadine hydrochloride is administered to a nursing woman.

8.4 Pediatric Use

The recommended doses of fexofenadine hydrochloride in pediatric patients 6 months to 11 years of age are based on cross-study comparison of the pharmacokinetics of fexofenadine in adults and pediatric subjects and on the safety profile of fexofenadine hydrochloride in both adult and pediatric subjects at doses equal to or higher than the recommended doses. The safety and effectiveness of fexofenadine hydrochloride in pediatric patients under 6 months of age have not been established.

The safety of fexofenadine hydrochloride is based on the administration of fexofenadine hydrochloride tablets at a dose of 30 mg twice daily demonstrated in 438 pediatric subjects 6 years to 11 years of age in 2 placebo-controlled 2 week seasonal allergic rhinitis trials. The safety of fexofenadine hydrochloride at doses of 15 mg and 30 mg given once and twice a day has been demonstrated in 969 pediatric subjects (6 months to 5 years of age) with allergic rhinitis in 3 pharmacokinetic studies and 3 safety studies. The safety of fexofenadine hydrochloride for the treatment of chronic idiopathic urticaria in subjects 6 months to 11 years of age is based on cross-study comparison of the pharmacokinetics of fexofenadine hydrochloride in adult and pediatric subjects and on the safety profile of fexofenadine in both adult and pediatric subjects at doses equal to or higher than the recommended dose.

The effectiveness of fexofenadine hydrochloride for the treatment of seasonal allergic rhinitis in subjects 6 to 11 years of age was demonstrated in 1 trial (n = 411) in which fexofenadine hydrochloride tablets 30 mg twice daily significantly reduced total symptom scores compared to placebo, along with extrapolation of demonstrated efficacy in subjects aged 12 years and above, and the pharmacokinetic comparisons in adults and children. The effectiveness of fexofenadine hydrochloride 30 mg twice daily for the treatment of seasonal allergic rhinitis in patients 2 to 5 years of age is based on the pharmacokinetic comparisons in adult and pediatric subjects and an extrapolation of the demonstrated efficacy of fexofenadine hydrochloride in adult subjects with this condition and the likelihood that the disease course, pathophysiology, and the drug’s effect are substantially similar in pediatric patients to those in adult patients. The effectiveness of fexofenadine hydrochloride for the treatment of chronic idiopathic urticaria in patients 6 months to 11 years of age is based on the pharmacokinetic comparisons in adults and children and an extrapolation of the demonstrated efficacy of fexofenadine hydrochloride in adults with this condition and the likelihood that the disease course, pathophysiology and the drug’s effect are substantially similar in children to that of adult patients. Administration of a 15 mg dose of fexofenadine hydrochloride to pediatric subjects 6 months to less than 2 years of age and a 30 mg dose to pediatric subjects 2 to 11 years of age produced exposures comparable to those seen with a dose of 60 mg administered to adults.

8.5 Geriatric Use

Clinical studies of fexofenadine hydrochloride tablets and capsules did not include sufficient numbers of subjects aged 65 years and over to determine whether this population responds differently from younger subjects. Other reported clinical experience has not identified differences in responses between the geriatric and younger subjects. This drug is known to be substantially excreted by the kidney, and the risk of toxic reactions to this drug may be greater in patients with impaired renal function. Because elderly patients are more likely to have decreased renal function, care should be taken in dose selection, and it may be useful to monitor renal function [see Clinical Pharmacology (12.3)].

8.6 Renal Impairment

Based on increases in bioavailability and half-life, a dose of 60 mg once daily is recommended as the starting dose in adult patients with decreased renal function (mild, moderate or severe renal impairment). For pediatric patients with decreased renal function (mild, moderate or severe renal impairment), the recommended starting dose of fexofenadine is 30 mg once daily for patients 2 to 11 years of age and 15 mg once daily for patients 6 months to less than 2 years of age [see Clinical Pharmacology (12.3)].

8.7 Hepatic Impairment

The pharmacokinetics of fexofenadine hydrochloride in subjects with hepatic impairment did not differ substantially from that observed in healthy subjects.

10 OVERDOSAGE

Dizziness, drowsiness, and dry mouth have been reported with fexofenadine hydrochloride overdose. Single doses of fexofenadine hydrochloride up to 800 mg (6 healthy subjects at this dose level), and doses up to 690 mg twice daily for 1 month (3 healthy subjects at this dose level) or 240 mg once daily for 1 year (234 healthy subjects at this dose level) were administered without the development of clinically significant adverse events as compared to placebo.

In the event of overdose, consider standard measures to remove any unabsorbed drug. Symptomatic and supportive treatment is recommended. Following administration of terfenadine, hemodialysis did not effectively remove fexofenadine, the major active metabolite of terfenadine, from blood (up to 1.7% removed).

No deaths occurred at oral doses of fexofenadine hydrochloride up to 5000 mg/kg in mice (110 times the maximum recommended daily oral dose in adults and children based on mg/m^2) and up to 5000 mg/kg in rats (230 times the maximum recommended daily oral dose in adults and 210 times the maximum recommended daily oral dose in children based on mg/m^2). Additionally, no clinical signs of toxicity or gross pathological findings were observed. In dogs, no evidence of toxicity was observed at oral doses up to 2000 mg/kg (300 times the maximum recommended daily oral dose in adults and 280 times the maximum recommended daily oral dose in children based on mg/m^2).

11 DESCRIPTION

Fexofenadine hydrochloride, the active ingredient of fexofenadine hydrochloride tablets, is a histamine H1-receptor antagonist with the chemical name (±)-4-[1-hydroxy-4-[4-(hydroxydiphenylmethyl)-1-piperidinyl]-butyl]-α, α-dimethyl benzeneacetic acid hydrochloride. It has the following chemical structure:

C32H39NO4•HCl M.W. 538.13

Fexofenadine hydrochloride is a white to off-white crystalline powder. It is freely soluble in methanol and ethanol, slightly soluble in chloroform and water, and insoluble in hexane. Fexofenadine hydrochloride is a racemate and exists as a zwitterion in aqueous media at physiological pH.

Fexofenadine hydrochloride is formulated as a tablet for oral administration. Each tablet contains 30, 60, or 180 mg fexofenadine hydrochloride (depending on the dosage strength) and the following excipients: colloidal silicon dioxide, croscarmellose sodium, hypromellose, iron oxide black, iron oxide red, iron oxide yellow, lactose monohydrate, magnesium stearate, microcrystalline cellulose, polyethylene glycol, povidone, and titanium dioxide.

Fexofenadine hydrochloride tablets meet USP Dissolution Test 3.

12 CLINICAL PHARMACOLOGY

12.1 Mechanism of Action

Fexofenadine hydrochloride, the major active metabolite of terfenadine, is an antihistamine with selective H1-receptor antagonist activity. Both enantiomers of fexofenadine hydrochloride displayed approximately equipotent antihistaminic effects. Fexofenadine hydrochloride inhibited antigen-induced bronchospasm in sensitized guinea pigs and histamine release from peritoneal mast cells in rats. The clinical significance of these findings is unknown. In laboratory animals, no anticholinergic or alpha1-adrenergic blocking effects were observed. Moreover, no sedative or other central nervous system effects were observed. Radiolabeled tissue distribution studies in rats indicated that fexofenadine does not cross the blood-brain barrier.

12.2 Pharmacodynamics

Wheal and Flare: Human histamine skin wheal and flare studies in adults following single and twice daily doses of 20 and 40 mg fexofenadine hydrochloride demonstrated that the drug exhibits an antihistamine effect by 1 hour, achieves maximum effect at 2 to 3 hours, and an effect is still seen at 12 hours. There was no evidence of tolerance to these effects after 28 days of dosing. The clinical significance of these observations is unknown.

Histamine skin wheal and flare studies in 7 to 12 year old subjects showed that following a single dose of 30 or 60 mg, antihistamine effect was observed at 1 hour and reached a maximum by 3 hours. Greater than 49% inhibition of wheal area, and 74% inhibition of flare area were maintained for 8 hours following the 30 and 60 mg dose.

No statistically significant increase in mean QTc interval compared to placebo was observed in 714 adult subjects with seasonal allergic rhinitis given fexofenadine hydrochloride capsules in doses of 60 to 240 mg twice daily for 2 weeks. Pediatric subjects from 2 placebo-controlled trials (n = 855) treated with up to 60 mg fexofenadine hydrochloride twice daily demonstrated no significant treatment- or dose-related increases in QTc. In addition, no statistically significant increase in mean QTc interval compared to placebo was observed in 40 healthy adult subjects given fexofenadine hydrochloride as an oral solution at doses up to 400 mg twice daily for 6 days, or in 230 healthy adult subjects given fexofenadine hydrochloride 240 mg once daily for 1 year. In subjects with chronic idiopathic urticaria, there were no clinically relevant differences for any ECG intervals, including QTc, between those treated with fexofenadine hydrochloride 180 mg once daily (n = 163) and those treated with placebo (n = 91) for 4 weeks.

12.3 Pharmacokinetics

The pharmacokinetics of fexofenadine hydrochloride in subjects with seasonal allergic rhinitis and subjects with chronic urticaria were similar to those in healthy subjects.

Absorption:

Fexofenadine hydrochloride was absorbed following oral administration of a single dose of two 60 mg capsules to healthy male subjects with a mean time to maximum plasma concentration occurring at 2.6 hours post-dose. After administration of a single 60 mg capsule to healthy adult subjects, the mean maximum plasma concentration (Cmax) was 131 ng/mL. Following single dose oral administrations of either the 60 and 180 mg tablet to healthy adult male subjects, mean Cmax were 142 and 494 ng/mL, respectively. The tablet formulations are bioequivalent to the capsule when administered at equal doses. Fexofenadine hydrochloride pharmacokinetics are linear for oral doses up to a total daily dose of 240 mg (120 mg twice daily). The administration of the 60 mg capsule contents mixed with applesauce did not have a significant effect on the pharmacokinetics of fexofenadine in adults. Coadministration of 180 mg fexofenadine hydrochloride tablet with a high fat meal decreased the mean area under the curve (AUC) and (Cmax) of fexofenadine by 21 and 20% respectively.

Distribution:

Fexofenadine hydrochloride is 60% to 70% bound to plasma proteins, primarily albumin and α1-acid glycoprotein.

Metabolism:

Approximately 5% of the total dose of fexofenadine hydrochloride was eliminated by hepatic metabolism.

Elimination:

The mean elimination half-life of fexofenadine was 14.4 hours following administration of 60 mg twice daily in healthy adult subjects.

Human mass balance studies documented a recovery of approximately 80% and 11% of the [^14C] fexofenadine hydrochloride dose in the feces and urine, respectively. Because the absolute bioavailability of fexofenadine hydrochloride has not been established, it is unknown if the fecal component represents primarily unabsorbed drug or is the result of biliary excretion.

Special Populations:

Pharmacokinetics in renally and hepatically impaired subjects and geriatric subjects, obtained after a single dose of 80 mg fexofenadine hydrochloride, were compared to those from healthy subjects in a separate study of similar design.

Renally Impaired:

In subjects with mild to moderate (creatinine clearance 41 to 80 mL/min) and severe (creatinine clearance 11 to 40 mL/min) renal impairment, peak plasma concentrations of fexofenadine were 87% and 111% greater, respectively, and mean elimination half-lives were 59% and 72% longer, respectively, than observed in healthy subjects. Peak plasma concentrations in subjects on dialysis (creatinine clearance ≤ 10 mL/min) were 82% greater and half-life was 31% longer than observed in healthy subjects. Based on increases in bioavailability and half-life, a dose of 60 mg once daily is recommended as the starting dose in adult patients with decreased renal function. For pediatric patients with decreased renal function, the recommended starting dose of fexofenadine is 30 mg once daily for patients 2 to 11 years of age and 15 mg once daily for patients 6 months to less than 2 years of age.

Hepatically Impaired:

The pharmacokinetics of fexofenadine hydrochloride in subjects with hepatic impairment did not differ substantially from that observed in healthy subjects.

Geriatric Subjects:

In older subjects (≥ 65 years old), peak plasma levels of fexofenadine were 99% greater than those observed in younger subjects (< 65 years old). Mean fexofenadine elimination half-lives were similar to those observed in younger subjects.

Pediatric Subjects:

A population pharmacokinetic analysis was performed with data from 77 pediatric subjects (6 months to 12 years of age) with allergic rhinitis and 136 adult subjects. The individual apparent oral clearance estimates of fexofenadine were on average 44% and 36% lower in pediatric subjects 6 to 12 years (n = 14) and 2 to 5 years of age (n = 21), respectively, compared to adult subjects.

Administration of a 15 mg dose of fexofenadine hydrochloride to pediatric subjects 6 months to less than 2 years of age and a 30 mg dose to pediatric subjects 2 to 11 years of age produced exposures comparable to those seen with a dose of 60 mg administered to adults.

Effect of Gender:

Across several trials, no clinically significant gender-related differences were observed in the pharmacokinetics of fexofenadine hydrochloride.

13 NONCLINICAL TOXICOLOGY

13.1 Carcinogenesis, Mutagenesis, Impairment of Fertility

The carcinogenic potential of fexofenadine was assessed using terfenadine studies with adequate fexofenadine exposure (based on plasma area-under-the-concentration vs. time [AUC] values). No evidence of carcinogenicity was observed in an 18 month study in mice and in a 24 month study in rats at oral doses up to 150 mg/kg of terfenadine (which led to fexofenadine exposures that were approximately 3 and 5 times the exposure at the maximum recommended daily oral dose of fexofenadine hydrochloride in adults [180 mg] and children [60 mg] respectively).

In in vitro (Bacterial Reverse Mutation, CHO/HGPRT Forward Mutation, and Rat Lymphocyte Chromosomal Aberration assays) and in vivo (Mouse Bone Marrow Micronucleus assay) tests, fexofenadine hydrochloride revealed no evidence of mutagenicity.

In rat fertility studies, dose-related reductions in implants and increases in postimplantation losses were observed at an oral dose of 150 mg/kg of terfenadine (which led to fexofenadine exposures that were approximately 3 times the exposure at the maximum recommended human daily oral dose of 180 mg of fexofenadine hydrochloride based on comparison of AUCs). In mice, fexofenadine hydrochloride produced no effect on male or female fertility at average oral doses up to 4438 mg/kg (which led to fexofenadine exposures that were approximately 13 times the exposure at the maximum recommended human daily oral dose of 180 mg of fexofenadine hydrochloride based on comparison of AUCs).

13.2 Animal Toxicology and/or Pharmacology

In dogs (30 mg/kg/orally twice daily for 5 days) and rabbits (10 mg/kg, intravenously over 1 hour), fexofenadine hydrochloride did not prolong QTc. In dogs, the plasma fexofenadine concentration was approximately 9 times the therapeutic plasma concentrations in adults receiving the maximum recommended human daily oral dose of 180 mg. In rabbits, the plasma fexofenadine concentration was approximately 20 times the therapeutic plasma concentration in adults receiving the maximum recommended human daily oral dose of 180 mg. No effect was observed on calcium channel current, delayed K^+ channel current, or action potential duration in guinea pig myocytes, or on the delayed rectifier K^+ channel cloned from human heart at concentrations up to 1 x 10^-5 M of fexofenadine.

14 CLINICAL STUDIES

14.1 Seasonal Allergic Rhinitis

Adults: In three 2 week, multicenter, randomized, double-blind, placebo-controlled trials in subjects 12 to 68 years of age with seasonal allergic rhinitis (n = 1634), fexofenadine hydrochloride 60 mg twice daily significantly reduced total symptom scores (the sum of the individual scores for sneezing, rhinorrhea, itchy nose/palate/throat, itchy/watery/red eyes) compared to placebo. Statistically significant reductions in symptom scores were observed following the first 60 mg dose, with the effect maintained throughout the 12 hour interval. In these studies, there was no additional reduction in total symptom scores with higher doses of fexofenadine hydrochloride up to 240 mg twice daily.

In one 2 week, multicenter, randomized, double-blind clinical trial in subjects 12 to 65 years of age with seasonal allergic rhinitis (n = 863), fexofenadine hydrochloride 180 mg once daily significantly reduced total symptom scores (the sum of the individual scores for sneezing, rhinorrhea, itchy nose/palate/throat, itchy/watery/red eyes) compared to placebo. Although the number of subjects in some of the subgroups was small, there were no significant differences in the effect of fexofenadine hydrochloride across subgroups of subjects defined by gender, age, and race. Onset of action for reduction in total symptom scores, excluding nasal congestion, was observed at 60 minutes compared to placebo following a single 60 mg fexofenadine hydrochloride dose administered to subjects with seasonal allergic rhinitis who were exposed to ragweed pollen in an environmental exposure unit. In 1 clinical trial conducted with fexofenadine hydrochloride 60 mg capsules, and in 1 clinical trial conducted with fexofenadine hydrochloride and pseudoephedrine hydrochloride extended-release tablets (12 hour formulation), onset of action was seen within 1 to 3 hours.

Pediatrics: Two 2 week, multicenter, randomized, placebo-controlled, double-blind trials in 877 pediatric subjects 6 to 11 years of age with seasonal allergic rhinitis were conducted at doses of 15, 30, and 60 mg (tablets) twice daily. In 1 of these 2 studies, conducted in 411 pediatric subjects, all 3 doses of fexofenadine hydrochloride significantly reduced total symptom scores (the sum of the individual scores for sneezing, rhinorrhea, itchy nose/palate/throat, itchy/watery/red eyes) compared to placebo, however, a dose-response relationship was not seen. The 60 mg twice daily dose did not provide any additional benefit over the 30 mg twice daily dose in pediatric subjects 6 to 11 years of age.

Administration of a 30 mg dose to pediatric subjects 2 to 11 years of age produced exposures comparable to those seen with a dose of 60 mg administered to adults [see Clinical Pharmacology (12.3)].

14.2 Chronic Idiopathic Urticaria

Two 4 week, multicenter, randomized, double-blind, placebo-controlled clinical trials compared four different doses of fexofenadine hydrochloride tablet (20, 60, 120, and 240 mg twice daily) to placebo in subjects aged 12 to 70 years with chronic idiopathic urticaria (n = 726). Efficacy was demonstrated by a significant reduction in mean pruritus scores (MPS), mean number of wheals (MNW), and mean total symptom scores (MTSS, the sum of the MPS and MNW score). Although all 4 doses were significantly superior to placebo, symptom reduction was greater and efficacy was maintained over the entire 4 week treatment period with fexofenadine hydrochloride doses of ≥ 60 mg twice daily. However, no additional benefit of the 120 or 240 mg fexofenadine hydrochloride twice daily dose was seen over the 60 mg twice daily dose in reducing symptom scores. There were no significant differences in the effect of fexofenadine hydrochloride across subgroups of subjects defined by gender, age, weight, and race.

In one 4 week, multicenter, randomized, double-blind, placebo-controlled clinical trial in subjects 12 years of age and older with chronic idiopathic urticaria (n = 259), fexofenadine hydrochloride 180 mg once daily significantly reduced the mean number of wheals (MNW), the mean pruritus score (MPS), and the mean total symptom score (MTSS, the sum of the MPS and MNW scores). Similar reductions were observed for mean number of wheals and mean pruritus score at the end of the 24 hour dosing interval. Symptom reduction was greater with fexofenadine hydrochloride 180 mg than with placebo. Improvement was demonstrated within 1 day of treatment with fexofenadine hydrochloride 180 mg and was maintained over the entire 4 week treatment period. There were no significant differences in the effect of fexofenadine hydrochloride across subgroups of subjects defined by gender, age, and race.

16 HOW SUPPLIED/STORAGE AND HANDLING

Repackaged by Aphena Pharma Solutions - TN.
See Repackaging Information for available configurations.

Fexofenadine hydrochloride tablets USP are available as follows:

30 mg – peach, capsule-shaped, film-coated tablets debossed with “93” on one side and “7251” on the other side, in bottles of 100.

60 mg – peach, round, film-coated tablets debossed with “93” on one side and “7252” on the other side, in bottles of 100 and 500.

180 mg – peach, round, film-coated tablets debossed with “93” on one side and “7253” on the other side, in bottles of 100 and 500.

Store at 20° to 25°C (68° to 77°F) [See USP Controlled Room Temperature]. Protect from excessive moisture.

Dispense in a tight, light-resistant container as defined in the USP, with a child-resistant closure (as required).

17 PATIENT COUNSELING INFORMATION

Provide the following information to patients and parents/caregivers of pediatric patients taking fexofenadine hydrochloride tablets:

- Fexofenadine hydrochloride tablets are prescribed for the relief of symptoms of seasonal allergic rhinitis or for the relief of symptoms of chronic idiopathic urticaria (hives). Instruct patients to take fexofenadine hydrochloride tablets only as prescribed. Do not exceed the recommended dose. If any untoward effects occur while taking fexofenadine hydrochloride tablets, discontinue use and consult a doctor.
- Patients who are hypersensitive to any of the ingredients should not use these products.
- Patients who are pregnant or nursing should use these products only if the potential benefit justifies the potential risk to the fetus or nursing infant.
- Advise patients and parents/caregivers of pediatric patients to store the medication in a tightly closed container in a cool, dry place, away from small children.
- Advise patients and parents/caregivers not to take fexofenadine hydrochloride tablets with fruit juices.
- Advise patients to take the fexofenadine hydrochloride tablets with water.

Maalox® is a registered trademark of AVENTIS PHARMACEUTICALS PRODUCTS INC.

Manufactured In Israel By:

TEVA PHARMACEUTICAL IND. LTD.

Jerusalem, 91010, Israel

Manufactured For:

TEVA PHARMACEUTICALS USA

Sellersville, PA 18960

Rev. G 10/2009

Repackaging Information

Please reference the How Supplied section listed above for a description of individual tablets or capsules. This drug product has been received by Aphena Pharma - TN in a manufacturer or distributor packaged configuration and repackaged in full compliance with all applicable cGMP regulations. The package configurations available from Aphena are listed below:

Count | 180mg
30 | 43353-244-30

Store between 20°-25°C (68°-77°F). See USP Controlled Room Temperature. Dispense in a tight light-resistant container as defined by USP. Keep this and all drugs out of the reach of children.

Repackaged by:
Cookeville, TN 38506
20120727KRW

PRINCIPAL DISPLAY PANEL - 180mg

NDC 43353-244 - Fexofenadine 180mg - Rx Only